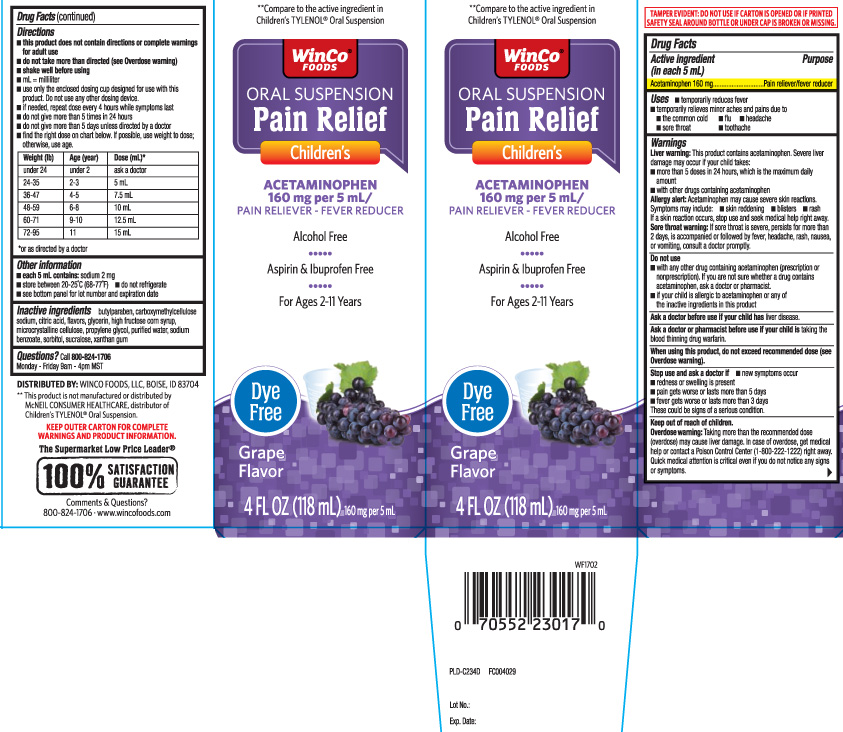 DRUG LABEL: Childrens Pain Relief Dye-Free
NDC: 67091-119 | Form: SUSPENSION
Manufacturer: WinCo Foods, LLC
Category: otc | Type: HUMAN OTC DRUG LABEL
Date: 20240411

ACTIVE INGREDIENTS: ACETAMINOPHEN 160 mg/5 mL
INACTIVE INGREDIENTS: ANHYDROUS CITRIC ACID; BUTYLPARABEN; GLYCERIN; CARBOXYMETHYLCELLULOSE SODIUM; CELLULOSE, MICROCRYSTALLINE; HIGH FRUCTOSE CORN SYRUP; WATER; SUCRALOSE; XANTHAN GUM; PROPYLENE GLYCOL; SODIUM BENZOATE; SORBITOL

Childrens Pain Relief Oral Suspension Dye-Free Grape

Active ingredient (in each 5 mL)

Acetaminophen 160 mg

Purpose

Pain reliever/fever reducer

Uses

- temporarily reduces fever
- relieves minor aches and pains due to:
  - the common cold
  - flu
  - headache
  - sore throat
  - toothache

Warnings

Liver warning: This product contains acetaminophen. Severe liver damage may occur if the child takes:

- more than 5 doses in 24 hours, which is maximum daily amount
- with other drugs containing acetaminophen

Allergy alert: Acetaminophen may cause severeskin reactions. Symptoms may include:

- skin reddening
- blisters
- rash

If a skin reaction occurs, stop use and seek medical help right away.

Sore throat warning: if sore throat is severe, persists for more than 2 days, or is accompanied or followed by fever, headache, rash, nausea, or vomiting, consult a doctor promptly.

Do not use

- with any other drug containing acetaminophen (prescription or non prescription). If you are not sure whether a drug contain acetaminophen, ask a doctor or pharmacist drugs.
- if your child is allergic to acetaminophen or any of the inactive ingredients in this product.

Ask a doctor before use if your child has

liver disease

Ask a doctor or pharmacist before use if your child is

taking the blood thinning drug warfarin

When using this product

do not exceed recommended dose (see overdose warning)

Stop use and ask a doctor if

- pain gets worse or lasts more than 5 days
- fever gets worse or lasts more than 3 days
- redness or swelling is present
- new symptoms occur
- These could be signs of a serious condition.

Keep out of reach of children.

Overdose warning: Taking more than the recommended dose (overdose) may cause liver damage. In case of overdose, get medical help or contact a poison control center right away. Quick medical attention is critical for adults as well as for children even if you do not notice any signs or symptoms.

Ask a doctor before use if your child has

liver disease

Ask a doctor or pharmacist before use if your child is

taking the blood thinning drug warfarin

When using this product

do not exceed recommended dose (see Overdose warning).

Stop use and ask a doctor if

- new symptoms occur
- redness or swelling is present
- pain gets worse or lasts more than 5 days
- fever gets worse or lasts more than 3 days

These could be signs of a serious condition.

Keep out of reach of children.

Overdose warning: Taking more than the recommended dose (overdose) may cause liver damage. In case of overdose, get medical help or contact a Poison Control Center (1-800-222-1222) right away. Quick medical attention is critical even if if you do not notice any signs or symptoms.

Directions

- this product does not contain directions or complete warnings for adult dose
- do not take more than directed (see Overdose warning)
- shake well before using
- mL = milliliter
- use only the enclosed dosing cup designed for use with this product. Do not use any other dosing device.
- if needed, repeat dose every 4 hours while symptoms last
- do not give more than 5 times in 24 hours
- do not give more than 5 days unless directed by a doctor
- find the right dose on chart below. If possible, use weight to dose; otherwise, use age.

Weight (lb) | Age (year) | Dose (mL)*
under 24 lbs | under 2 years | ask a doctor
24-35 lbs | 2-3 | 5 mL
36-47 lbs | 4-5 | 7.5 mL
48 - 59 lbs | 6-8 | 10 mL
60 - 71 lbs | 9-10 | 12.5 mL
72 - 95 lbs | 11 years | 15 mL

*or as directed by a doctor

Other information

- each 5 mL contains: sodium 2 mg
- store between 20-25oC(68-77oF)
- do not refrigerate
- see bottom panel for lot number and expiration date

Inactive ingredients

butylparaben, microcrystalline cellulose, carboxymethylcellulose sodium, citric acid,flavors, glycerin, high fructose corn syrup, propylene glycol, purified water, sodium benzoate, sorbitol,sucralose, xanthan gum

Questions?

Call 800-824-1706 Monday - Friday 9am - 4 pm MST

Principal Display Panel

**Compare to the active ingredient in Children's TYLENOL® Oral Suspension

ORAL SUSPENSION

Pain Relief

Children's

ACETAMINOPHEN 160 mg per 5 mL /

PAIN RELIEVER - FEVER REDUCER

Alcohol Free

Aspirin & Inuprofen Free

For Ages 2-11 Years

Dye Free

Grape Flavor

FL OZ (mL)

**This product is not manufactured or distributed by McNEIL CONSUMER HEALTHCARE, distributor of Children's TYLENOL® Oral Suspension.

KEEP OUTER CARTON FOR COMPLETE WARNINGS AMD PRODUCT INFORMATION.

DISTRIBUTED BY: WINCO FOODS, LLC BOISE, ID 83704

Comments or Question?

800-824-1706 www.wincofoods.com

Package label

WINCO FOODS Children's Pain Relief Dye Free Grape Flavor